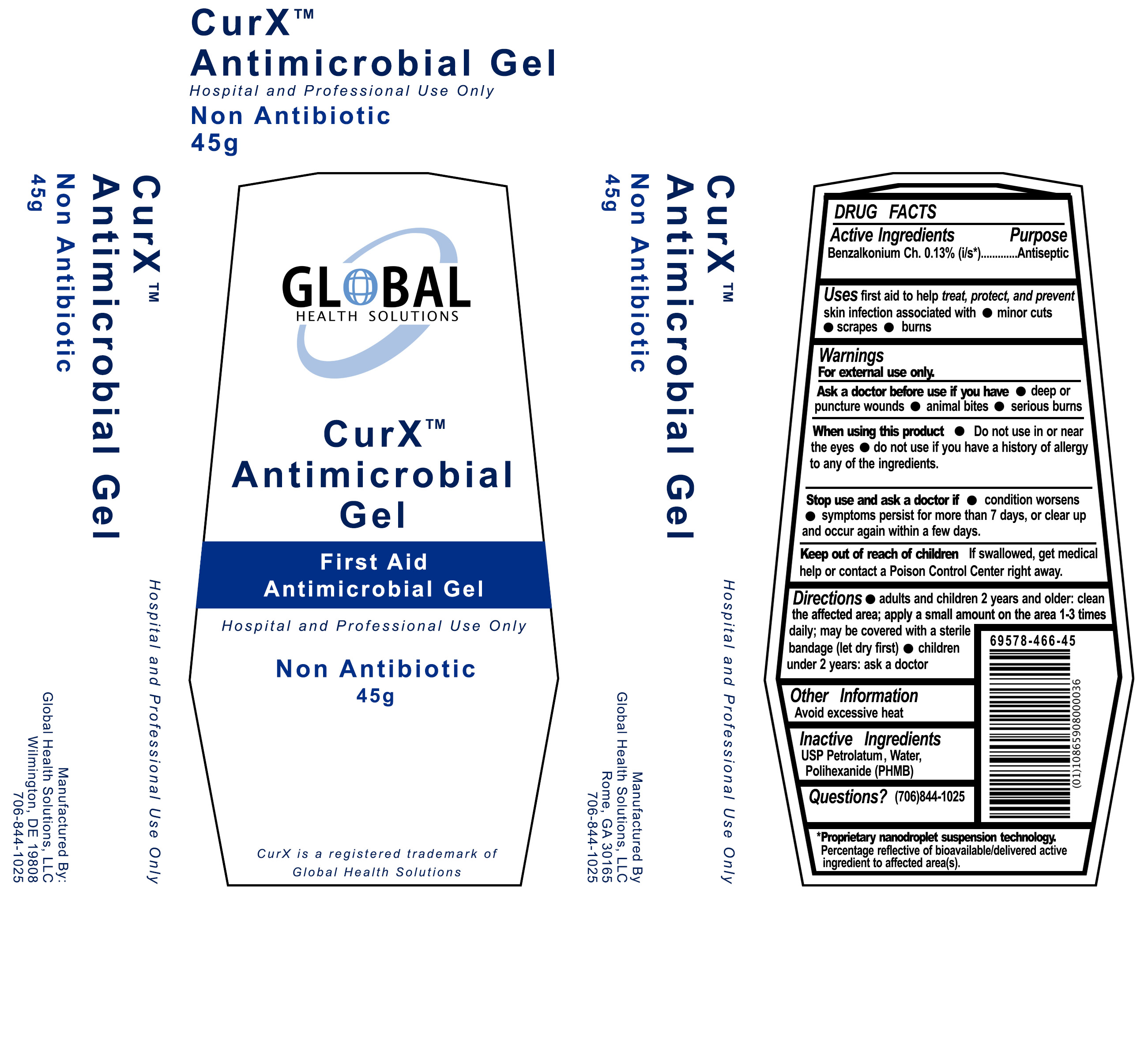 DRUG LABEL: CurX Antimicrobial Gel
NDC: 69578-466 | Form: GEL
Manufacturer: Global Health Solutions, LLC
Category: otc | Type: HUMAN OTC DRUG LABEL
Date: 20151028

ACTIVE INGREDIENTS: BENZALKONIUM CHLORIDE 0.13 g/100 g
INACTIVE INGREDIENTS: WATER; PETROLATUM; POLIHEXANIDE

DRUG FACTS

Active Ingredients

Benzalkonium Ch. 0.13% (i/s*)

Purpose

First Aid Antiseptic

Uses

first aid to to help treat, protect and prevent skin infection associated with

- minor cuts

- scrapes

- burns

Warnings

For external use only

Ask a doctor before use if you have

- deep or puncture wounds

- animal bites

- serious burns

When using this product

- Do not use in or near the eyes
- do not use if you have a history of allergy to any of the ingredients.

Stop use and ask a doctor if

- condition worsens
- symptoms persist for more than 7 days, or clear up and occur again within a few days.

Keep out of reach of children

If swallowed, get medical help or contact a Poison Control Center right away.

Directions

- adults and children 2 years and older: clean the affected area; apply a small amount on the area 1-3 times daily;may be covered with a sterile bandage (let dry first)

- children under 2 years: ask a doctor

Other Information

Avoid excessive heat

Inactive Ingredients

USP Petrolatum, Water, Polihexanide (PHMB)

Questions?

1-706-844-1025

Principal Display Panel

GLOBAL HEALTH SOLUTIONS, LLC

CurXTM Antimicrobial Gel

First Aid Antimicrobial Gel

Hospital and Professional Use Only

Non-Antibiotic

45 g

CurX is a registered trademark of Global Health Solutions

*Microdroplet Suspension Technology

*Proprietary microdroplet suspension technology. Percentage reflective of active ingredient bioavailability in solution.